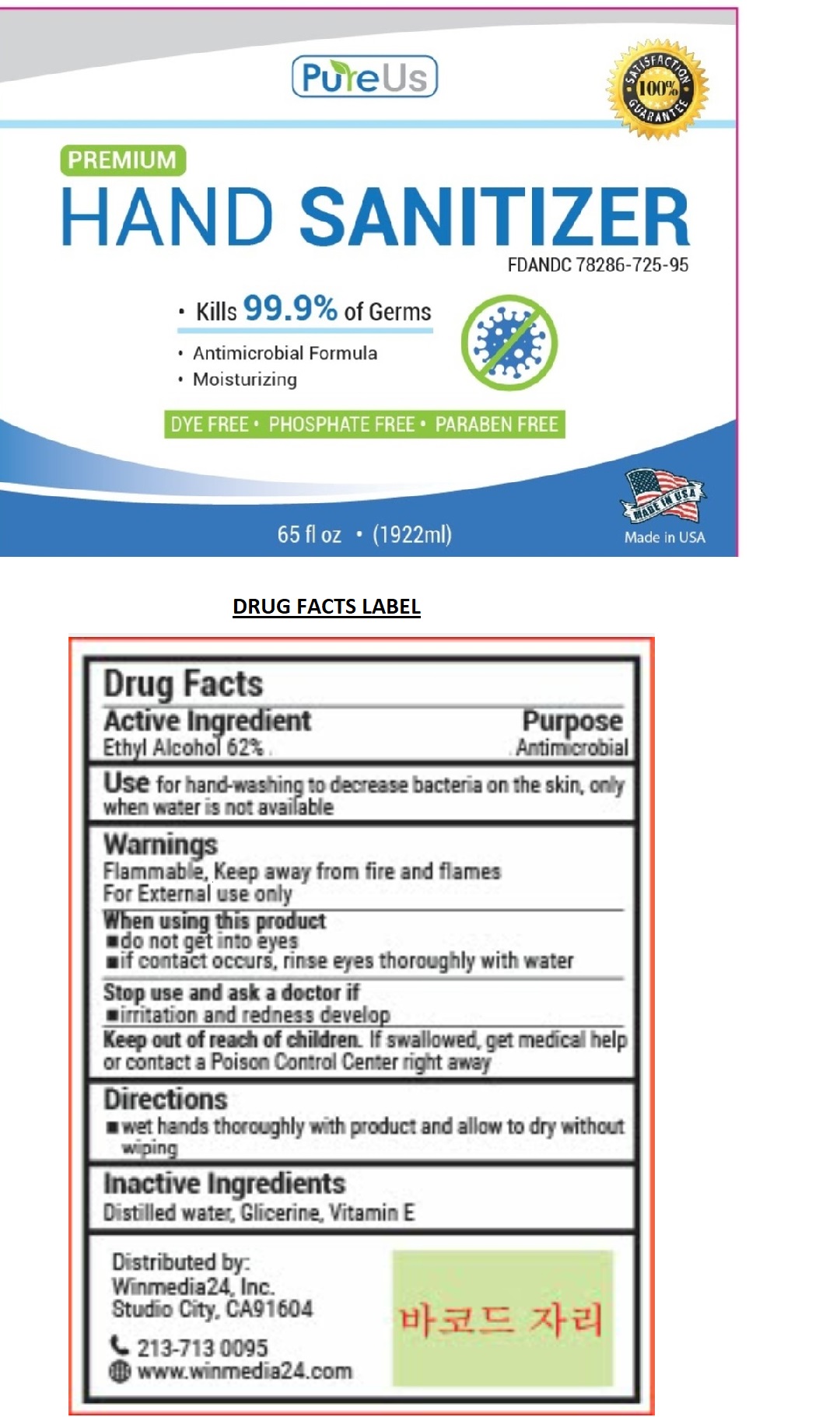 DRUG LABEL: PureUs
NDC: 78286-725 | Form: LIQUID
Manufacturer: Winmedia24
Category: otc | Type: HUMAN OTC DRUG LABEL
Date: 20200601

ACTIVE INGREDIENTS: ALCOHOL 62 mL/100 mL
INACTIVE INGREDIENTS: WATER; GLYCERIN; .ALPHA.-TOCOPHEROL

PureUs PREMIUM HAND SANITIZER

Active Ingredient

Ethyl Alcohol 62%

Purpose

Antimicrobial

Use

for hand-washing to decrease on the skin, only when water is not available

Warnings

Flammable, Keep away from fire and flames

For External use only

When using this product

▪do not get into eyes

▪if contact occurs, rinse eyes thoroughly with water

Stop use and ask a doctor if

▪irritation and redness develop

Keep out of reach of children. If swallowed, get medical help or contact a Poison Control Center right away

Directions

▪ wet hands thoroughly with product and allow to dry without wiping

Inactive Ingredients

Distilled water, Glicerine, Vitamin E

• Kills 99.9% of Germs

• Antimicrobial Formula

• Moisturizing

DYE FREE • PHOSPHATE FREE • PARABEN FREE

Made in USA

Distributed by:

Winmedia24, Inc.

Studio City, CA91604

213-713 0095

www.winmedia24.com